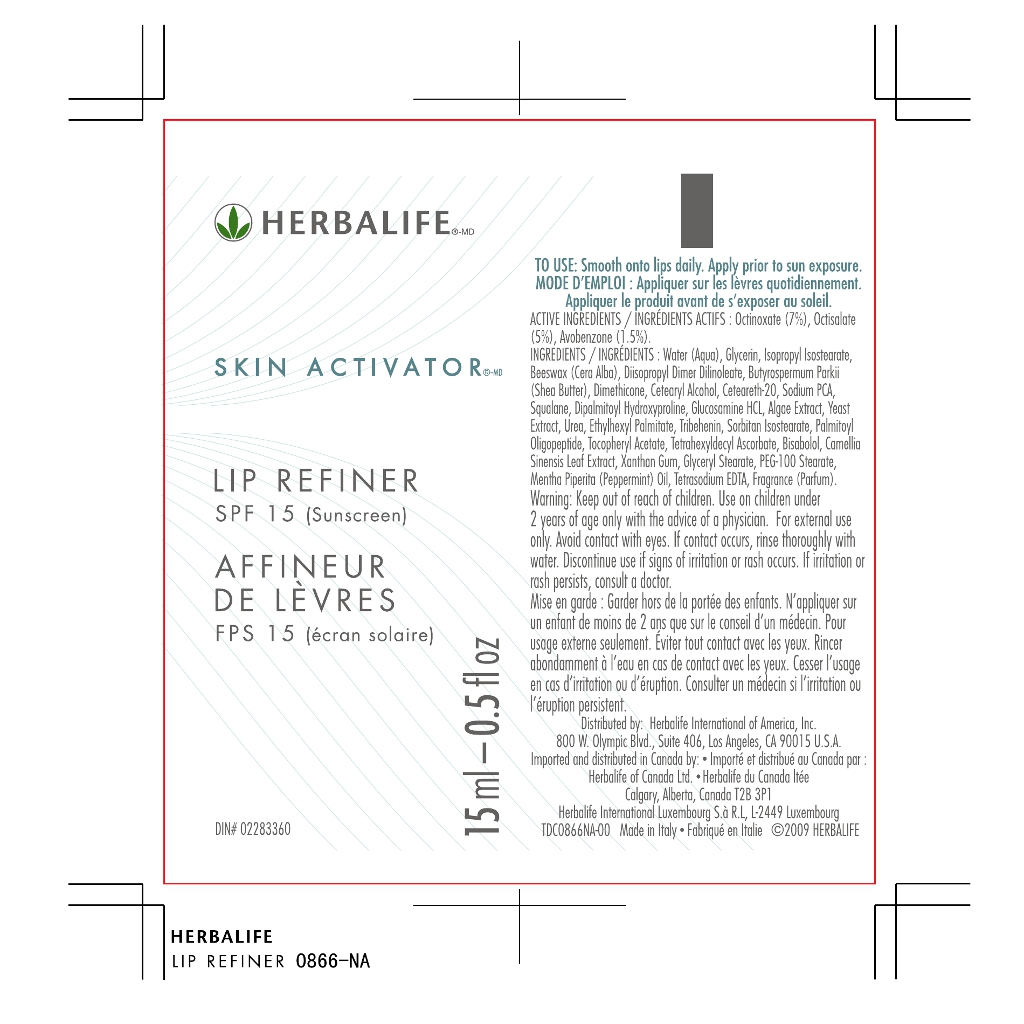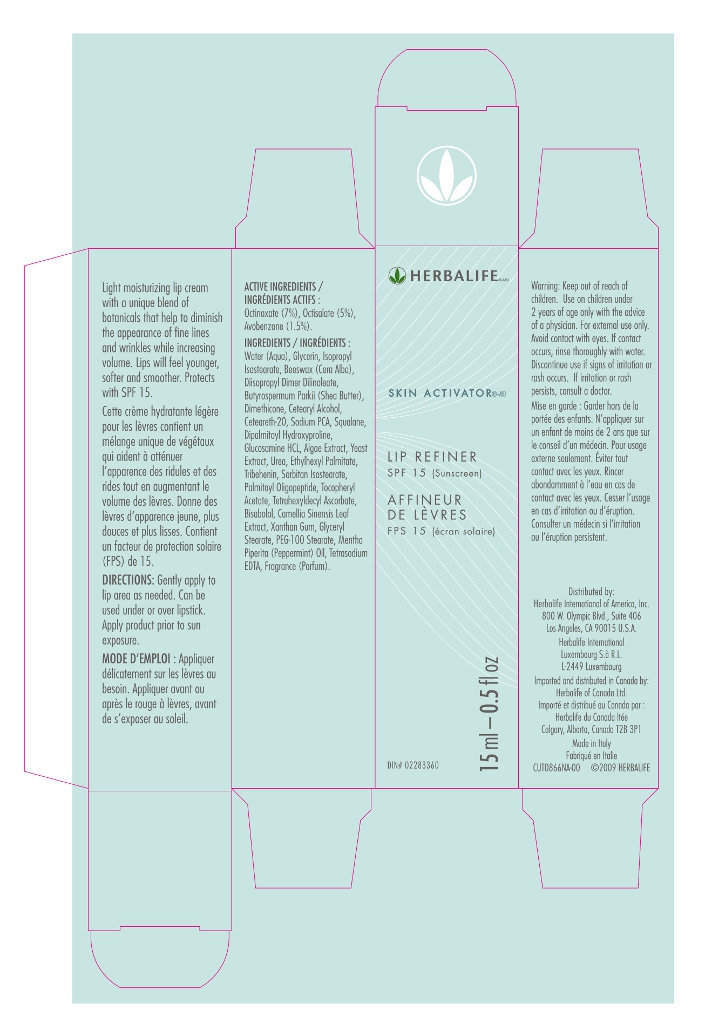 DRUG LABEL: Skin Activator
NDC: 63509-002 | Form: CREAM
Manufacturer: Cosmint Spa.
Category: otc | Type: HUMAN OTC DRUG LABEL
Date: 20111123

ACTIVE INGREDIENTS: Octinoxate 0.0661 g/1 mL; Octisalate 0.0472 g/1 mL; Avobenzone 0.0142 g/1 mL
INACTIVE INGREDIENTS: Water; Glycerin; ISOPROPYL ISOSTEARATE; Yellow wax; Diisopropyl Dilinoleate; Shea butter; Dimethicone; Cetostearyl Alcohol; Polyoxyl 20 Cetostearyl Ether; Sodium Pyrrolidone Carboxylate; Squalane; Dipalmitoyl hydroxyproline; Glucosamine hydrochloride; Laminaria digitata; Yeast; Urea ; Ethylhexyl palmitate; Tribehenin; Sorbitan isostearate; Palmitoyl oligopeptide; Alpha-Tocopherol Acetate; Tetrahexyldecyl ascorbate; Levomenol; Green Tea Leaf; Xanthan gum; Glyceryl Monostearate; PEG-100 Stearate; Peppermint oil; Edetate Sodium

Drug Facts

ACTIVE INGREDIENTS
Octinoxate (7%)
Octisalate (5%)
Avobenzone (1.5%)

DIRECTIONS
Smooth onto lips daily.
Apply prior to sun exposure

WARNINGS
For external use only.

Keep out of reach of children.
Use on children under 2 years of age only with the advice of physician.

WHEN USING

Avoid contact with eyes. If contact occurs, rinse thoroughly with water.

STOP USE

Discontinue use if signs of irritation or rush occurs. If irritation or rash persist, consult a doctor.

INACTIVE INGREDIENTS

Water
Glycerin
Isopropyl isostearate
Beeswax (cera alba)
Diisopropyl dimer dilinoleate
Butyrospermum parkii (shea) butter
Dimethicone
Cetearyl alcohol
Ceteareth 20
Sodium pca
Squalane
Dipalmitoyl hydroxyproline
Glucosamine hydrochloride
Algae extract
Yeast extract
Urea
Ethylhexyl palmitate
Tribehenin
Sorbitan isostearate
Palmitoyl oligopeptide
Tocopherol acetate
Tetrahexyldecyl ascorbate
Bisabolol
Camellia sinensis leaf extract
Xanthan gum
Glyceryl stearate
Peg 100 stearate
Mentha piperita (peppermint) oil
Tetrasodium edta
Fragrance (parfum)